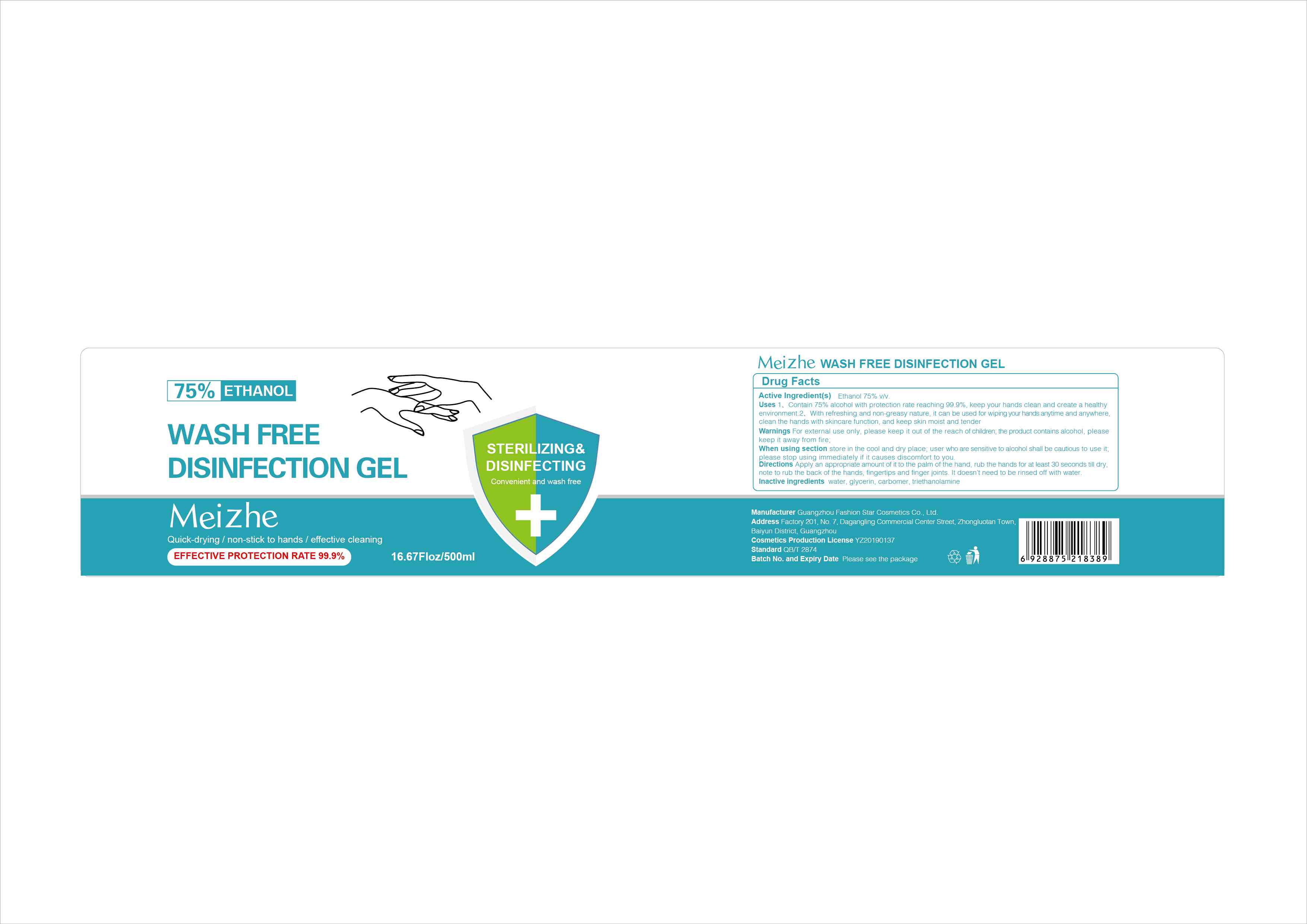 DRUG LABEL: WASH FREE DISINFECTION
NDC: 78305-005 | Form: GEL
Manufacturer: Guangzhou Fashion Star Cosmetics Co.,Ltd
Category: otc | Type: HUMAN OTC DRUG LABEL
Date: 20200523

ACTIVE INGREDIENTS: ALCOHOL 75 mL/100 mL
INACTIVE INGREDIENTS: TROLAMINE; GLYCERIN; CARBOMER HOMOPOLYMER, UNSPECIFIED TYPE; WATER

Guangzhou Fashion Star Cosmetics Co.,Ltd

Active Ingredient(s)

Ethanol 75% v/v

Purpose

/

Use

1、Contain 75% alcohol with protection rate reaching 99.9%, keep your hands clean and create a healthy environment.2、With refreshing and non-greasy nature, it can be used for wiping your hands anytime and anywhere, clean the hands with skincare function, and keep skin moist and tender

Warnings

For external use only, please keep it out of the reach of children; the product contains alcohol, please keep it away from fire;

Do not use

/

WHEN USING

When using section store in the cool and dry place; user who are sensitive to alcohol shall be cautious to use it; please stop using immediately if it causes discomfort to you.

STOP USE

please stop using immediately if it causes discomfort to you.

KEEP OUT OF REACH OF CHILDREN

please keep it out of the reach of children;

Directions

Apply an appropriate amount of it to the palm of the hand, rub the hands for at least 30 seconds till dry, note to rub the back of the hands, fingertips and finger joints. It doesn't need to be rinsed off with water.

Inactive ingredients

water, glycerin, carbomer, triethanolamine